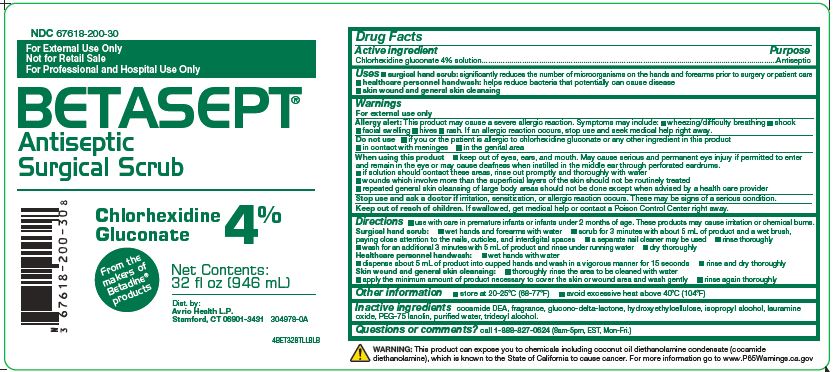 DRUG LABEL: BETASEPT
NDC: 67618-200 | Form: SOLUTION
Manufacturer: Atlantis Consumer Healthcare, Inc.
Category: otc | Type: HUMAN OTC DRUG LABEL
Date: 20251224

ACTIVE INGREDIENTS: Chlorhexidine Gluconate .04 mg/1 mL
INACTIVE INGREDIENTS: COCO DIETHANOLAMIDE; HYDROXYETHYL CELLULOSE (2000 CPS AT 1%); ISOPROPYL ALCOHOL; LAURAMINE OXIDE; WATER; TRIDECYL ALCOHOL; GLUCONOLACTONE; PEG-75 LANOLIN

BETASEPT Antiseptic Surgical Scrub
Chlorhexidine Gluconate 4%

Drug Facts
Active ingredient Purpose
Chlorhexidine gluconate 4% solution

Purpose
Antiseptic

Uses

- surgical hand scrub: significantly reducesthe number of microorganisms on the hands and forearms prior to surgery or patient care
- healthcare personnel handwash: helps reducebacteria that potentially can cause disease
- skin wound and general skin cleansing

Warnings
For external use only
Allergy alert: This product may cause a severe allergic reaction. Symptoms may include:

- wheezing/difficulty breathing
- Shock
- facial swelling
- hives
- rash.

If an allergic reaction occurs, stop use and seek medical help right away.

Do not use

- if you or the patient is allergic to chlorhexidine gluconateor any other ingredient in this product
- in contact with meninges
- in the genital area

When using this product

- keep out of eyes, ears, and mouth. May cause serious andpermanent eye injury if permitted to enter and remain in the eye ormay cause deafness when instilled in the middle ear through perforatedeardrums.
- if solution should contact these areas, rinse out promptlyand thoroughly with water
- wounds which involve more than the superficial layers ofthe skin should not be routinely treated
- repeated general skin cleansing of large body areas shouldnot be done except when advised by a health care provider

Stop use and ask a doctor if irritation,sensitization, or allergic reaction occurs. These may be signs ofa serious condition.

Keep out of reach of children. Ifswallowed, get medical help or contact a Poison Control Center rightaway.

Directions

- use with care in premature infants or infants under 2 months of age. These products may cause irritation or chemical burns.

INDICATIONS AND USAGE

Surgical hand scrub:

- wet hands and forearms with water
- scrub for 3 minutes with about 5 mL of product and a wetbrush, paying close attention to the nails, cuticles, and interdigitalspaces
- a separate nail cleaner may be used
- rinse thoroughly
- wash for an additional 3 minutes with 5 mL of product andrinse under running water
- dry thoroughly

DOSAGE AND ADMINISTRATION

Healthcare personnelhandwash:

- wet hands with water
- dispense about 5 mL of product into cupped hands and washin a vigorous manner for 15 seconds
- rinse and dry thoroughly

DOSAGE FORMS AND STRENGTHS

Skin wound and general skin cleansing:

- thoroughly rinse the area to be cleaned with water
- apply the minimum amount of product necessary to cover theskin or wound area and wash gently
- rinse again thoroughly

Other information

- store at 20-25°C (68-77°F)
- avoid excessive heat above 40°C (104°F)

INACTIVE INGREDIENT

Inactive ingredients cocamide DEA, fragrance, glucono-delta-lactone, hydroxyethylcellulose, isopropyl alcohol, lauramine oxide, PEG-75 lanolin, purified water, tridecyl alcohol

Questions or comments? call 1-888-827-0624 (8am-5pm, EST, Mon-Fri.)

WARNING: This product can expose you to chemicals including coconut oil diethanolamine condensate (cocamide diethanolamine), which is known to the State of California to cause cancer. For more information go to www.P65Warnings.ca.gov

Dist. by: Avrio Health L.P. Stamford, CT 06901-3431

304978-0A

PACKAGE LABEL

BETASEPT
Antiseptic Surgical Scrub
NDC: 67618–200–30